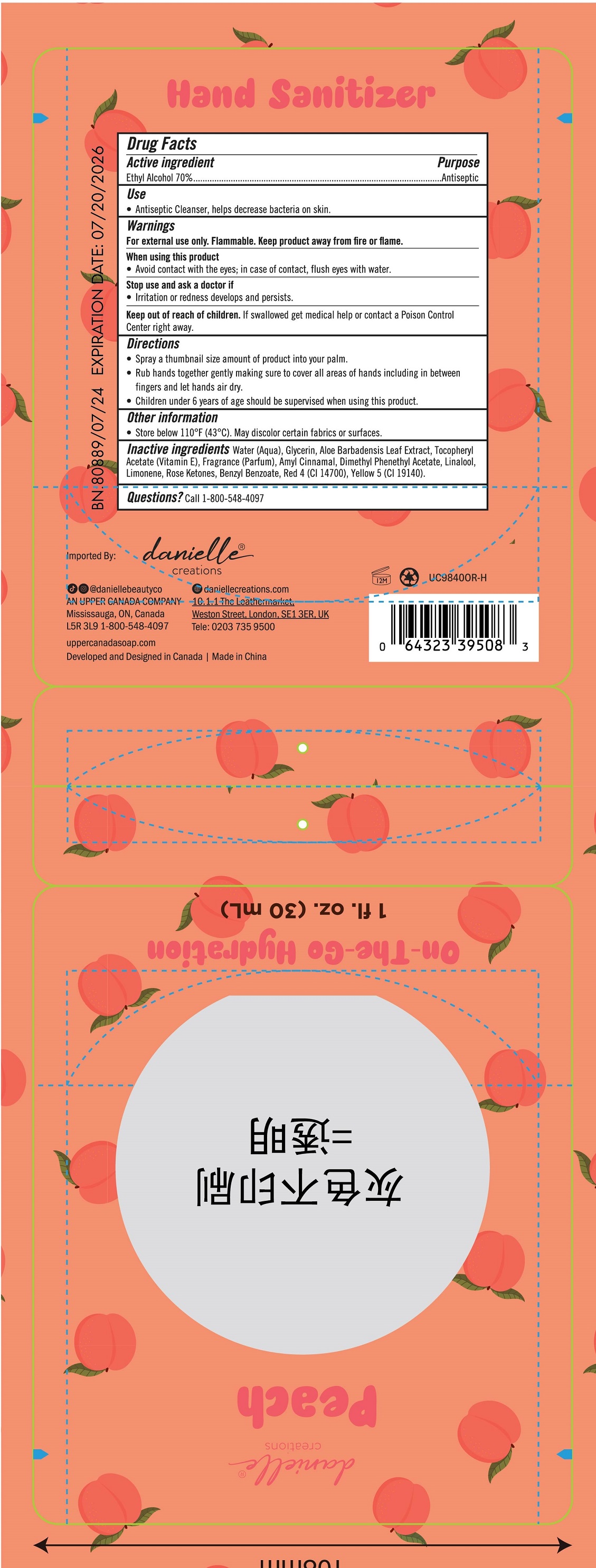 DRUG LABEL: Danielle Creations Hand Sanitizer - Peach
NDC: 56136-449 | Form: SPRAY
Manufacturer: Ganzhou Olivee Cosmetic Co., Ltd.
Category: otc | Type: HUMAN OTC DRUG LABEL
Date: 20240910

ACTIVE INGREDIENTS: ALCOHOL 70 mL/100 mL
INACTIVE INGREDIENTS: WATER; GLYCERIN; .ALPHA.-TOCOPHEROL ACETATE, D-; .ALPHA.-AMYLCINNAMALDEHYDE; BENZYL BENZOATE; FD&C RED NO. 4; FD&C YELLOW NO. 5

30ml peach hand sanitizer

Active ingredient

Ethyl Alcohol 70%

Purpose

Antiseptic

Use

Antiseptic cleanser, helps decrease bacteria on hands.

Warnings

For external use only.

Flammable.Keep product away from fire or flame.

When using this product

avoid contact with eyes; in case of contact, flush eyes with water.

Stop use and ask a doctor if

irritation or redness develops and persists.

Keep out of reach of children.

If swallowed, get medical help or contact a Poison Control Center right away.

Directions

- Spray a tubnail size amount of product into your palm.
- Rub hands together gently making sure to cover all areas of hands including in between fingers and let hands air dry.
- children under 6 years of age should be supervised when using this product.

Inactive ingredients

Water (Aqua), Glycerin, Aloe Barbadensis Leaf Extract, Tocopheryl Acetate (Vitamin E), Fragrance (Parfum) Amyl Cinnamal, Dimethyl Phenethyl Acetate, Linalool, Limonene, Rose Ketones, Benzyl Benzoate, Red 4 (Cl 14700), Yellow 5 (Cl 19140).

Store below 110℉（43℃）. May discolor certain fabrics or surfaces.

Questions? 1-800-548-4097